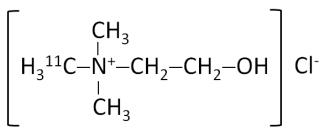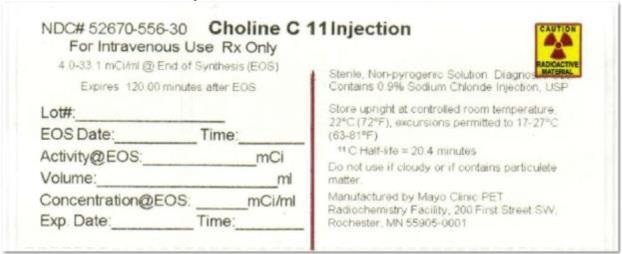 DRUG LABEL: Choline C 11
NDC: 52670-556 | Form: INJECTION
Manufacturer: Mayo Clinic
Category: prescription | Type: HUMAN PRESCRIPTION DRUG LABEL
Date: 20251226

ACTIVE INGREDIENTS: CHOLINE C-11 33.1 mCi/1 mL
INACTIVE INGREDIENTS: SODIUM CHLORIDE

HIGHLIGHTS OF PRESCRIBING INFORMATION

These highlights do not include all the information needed to use Choline C 11 Injectionsafely and effectively. See full prescribing information for Choline C 11 Injection.
Choline C 11 Injection, for intravenous use
Initial U.S. Approval: 2012

1 INDICATIONS AND USAGE

Choline C 11 Injection is a radioactive diagnostic agent for positron emission tomography (PET) imaging of patients with suspected prostate cancer recurrence and non-informative bone scintigraphy, computerized tomography (CT) or magnetic resonance imaging. In these patients,^11 C-choline PET imaging may help identify potential sites of prostate cancer recurrence for subsequent histologic confirmation. Suspected prostate recurrence is based upon elevated blood prostate specific antigen (PSA) levels following initial therapy. In clinical studies, images were produced with PET/CT coregistration.

Limitation of Use:^11 C-choline PET imaging is not a replacement for histologic verification of recurrent prostate cancer (1).

2 DOSAGE AND ADMINISTRATION

- Aseptically withdraw Choline C 11 Injection from its container and administer 370 – 740 MBq (10 – 20 mCi) as a bolus intravenous injection. The radioactivity dose (370 – 740 MBq, 10 – 20 mCi) is chosen based on patient body dimensions and the characteristics of the image acquisition system (2.1).
- Initiate imaging immediately after administration of Choline C 11 Injection and acquire static emission images 0 – 15 minutes from the time of injection (2.5).
- The effective radiation absorbed dose from 740 MBq (20 mCi) dose of Choline C 11 Injection is approximately 3.22 mSv (0.32 rem) in an adult (2.4).
- Image interpretation: Refer to full prescribing information (2.5).

3 DOSAGE FORMS AND STRENGTHS

- Choline C 11 Injection contains 148 – 1,225 MBq (4 – 33.1 mCi) per milliliter of ^11C-choline at end of synthesis calibration time in aqueous 0.9% sodium chloride solution (3).

4 CONTRAINDICATIONS

None (4).

5 WARNINGS AND PRECAUTIONS

- Imaging errors have been reported; blood PSA levels < 2 ng/mL have been associated with poor imaging performance (5.1).
- Allergic reactions: have emergency resuscitation equipment and personnel readily available (5.2).
- Radiation risk: Choline C 11 Injection contributes to a patient’s long-term cumulative radiation exposure. Ensure safe handling to protect the patient and health care worker (5.3).

6 ADVERSE REACTIONS

Exclusive of an uncommon, mild injection site reaction, no other adverse reactions have been reported (6).

To report SUSPECTED ADVERSE REACTIONS, contact Division of Nuclear Medicine, Department of Radiology, Mayo Clinic at 507-284-2511 or FDA at 1-800-FDA-1088 or www.fda.gov/medwatch

7 DRUG INTERACTIONS

Colchicine and androgen-deprivation therapeutic drugs may interfere with ^11C-choline PET/CT imaging performance (5.1).

FULL PRESCRIBING INFORMATION

1 INDICATIONS AND USAGE

Choline C 11 Injection is indicated for positron emission tomography (PET) imaging of patients with suspected prostate cancer recurrence and non-informative bone scintigraphy, computerized tomography (CT) or magnetic resonance imaging (MRI). In these patients,^11 C-choline PET imaging may help identify potential sites of prostate cancer recurrence for subsequent histologic confirmation. Suspected prostate recurrence is based upon elevated blood prostate specific antigen (PSA) levels following initial therapy. In clinical studies, images were produced with PET/CT coregistration.

Limitation of Use:^11 C-choline PET imaging is not a replacement for histologic verification of recurrent prostate cancer.

2 DOSAGE AND ADMINISTRATION

2.1 Radiation Safety – Drug Handling

Choline C 11 Injection is a radioactive drug and should be handled with appropriate safety measures to minimize radiation exposure during administration. Use waterproof gloves and effective shielding when handling Choline C 11 Injection. Radiopharmaceuticals, including Choline C 11 Injection, should only be used by or under the control of physicians who are qualified by specific training and experience in the safe use and handling of radioactive materials, and whose experience and training have been approved by the appropriate governmental agency authorized to license the use of radionuclides.

2.2 Recommended Dose and Administration Instructions

The recommended dose is 370 – 740 MBq (10 – 20 mCi) administered as a bolus intravenous injection. The radioactivity dose (370 – 740 MBq, 10 – 20 mCi) is chosen based on patient body dimensions and the characteristics of the image acquisition system

- Inspect Choline C 11 Injection visually for particulate matter and discoloration before administration. Do not use the drug if the solution contains particulate matter or is discolored.
- Aseptically withdraw Choline C 11 Injection from its container and administer the drug as a bolus through a peripheral venous catheter.
- Dispose of any unused drug in a safe manner, in compliance with applicable regulations.

2.3 Patient Preparation

Prior to administration of Choline C 11 Injection:

- Fasting for at least six hours is recommended to minimize the potential for dietary choline interference with radioactivity uptake in tissue.
- Ensure that the patient is well hydrated and encourage voiding when imaging is completed.

2.4 Radiation Dosimetry

The estimated radiation absorbed doses for adults from intravenous injection of Choline C 11 Injection are shown in Table 1. These estimates are calculated from data in Tolvanen^1 and using OLINDA/EXM (Organ Level Internal Dose Assessment/Exponential Modeling) software from Vanderbilt University.^2

Table 1: Estimated Radiation Absorbed Dose Per Unit Activity for Adults, Choline C 11 Injection
Organ/Tissue | Mean Absorbed Dose Per Unit Administered Activity (μ Gy/MBq) b
Adrenals | 3.59
Bone - Osteogenic Cells | 4.81
Bone - Red Marrow | 1.90
Brain | 1.16
Breast | 1.39
Gallbladder Wall | 4.54
GIa – Lower Large Intestine Wall | 1.81
GIa - Small Intestine | 2.35
GIa - Stomach Wall | 6.00
GIa – Upper Large Intestine Wall | 6.41
Heart wall | 3.43
Kidneys | 20.62
Liver | 20.11
Lungs | 4.59
Muscle | 2.54
Ovaries | 2.02
Pancreas | 29.19
Skin | 1.22
Spleen | 9.16
Testes | 1.36
Thymus | 1.69
Thyroid | 1.49
Urinary Bladder Wall | 3.41
Uterus | 1.96
Total body | 2.97
Effective Dose (μSv/MBq)c | 4.35

a Gastrointestinal
b Assumed radiation weighting factor, wr, (formerly defined as quality factor, Q) of 1 for conversion of absorbed dose (Gray or rad) to dose equivalent (Sieverts or rem) for C 11. To obtain radiation absorbed dose in rad/mCi from the above table, multiply the dose in μGy/MBq by 0.0037, (e.g., 3.59 μGy/MBq × 0.0037 = 0.0133 rad/mCi).
c Radiation tissue weighting factors, wT, used in the calculation of effective dose are from 1990 Recommendations of the International Commission on Radiological Protection, ICRP Publication 60 (1991). To obtain radiation absorbed dose in rem/mCi from above table, multiply the dose in μGy/MBq by 0.0037, (e.g., 4.35 μGy/MBq × 0.0037 = 0.0161 rem/mCi).

The effective dose resulting from a 740 MBq (20 mCi) dosage of Choline C 11 Injection is 3.22 mSv in an adult, (740 × 4.35 = 3219 μSv = 3.2 mSv). The use of a CT scan to calculate attenuation correction for reconstruction of^11C-choline images (as done in PET/CT imaging) will add radiation exposure. Based upon current scanning techniques, an effective dose of 5.8 mSv would be added from CT scanning. The actual radiation dose is operator, scanner, and patient dependent. The total radiation exposure from^11C-choline administration and subsequent scan on a PET/CT scanner is estimated to be 9.0 mSv (3.2 mSv + 5.8 mSv).

2.5 Imaging Guidelines

- Initiate image acquisition immediately after administration of Choline C 11 Injection. Imaging is typically performed from the base of the pelvis to the base of the skull.
- Acquire static emission images 0 – 15 minutes from the time of injection.
- Localized uptake of^11C-choline in a site suspicious for prostate cancer recurrence (a positive image) is determined by comparison of the anatomical relationship of concentrated radioactivity to the neighboring tissue background, exclusive of the radioactivity physiologically accumulated within the pancreas, liver, spleen, kidney and colon.

3 DOSAGE FORMS AND STRENGTHS

Choline C 11 Injection contains 148 – 1,225 MBq (4 – 33.1 mCi) per milliliter of^11C-choline at end of synthesis (EOS) calibration time in aqueous 0.9% sodium chloride solution.

4 CONTRAINDICATIONS

None.

5 WARNINGS AND PRECAUTIONS

5.1 Imaging Errors

Imaging errors have been reported with^11C-choline PET and PET/CT imaging. A negative image does not rule out the presence of recurrent prostate cancer and a positive image does not confirm the presence of recurrent cancer. 11C-choline uptake is not specific for prostate cancer and may occur with other types of cancer (such as lung carcinoma and brain tumors). Clinical correlation, including histopathological evaluation of the suspected recurrence site, is essential to proper use of the PET imaging information.

- Blood PSA levels < 2 ng/mL have been associated with poor performance of^11C-choline PET imaging (higher numbers of false positive and false negative results) [see Clinical Studies (14)].
- Tissue inflammation as well as prostatic hyperplasia have been associated with false positive^11C-choline PET images.
- Concomitant colchicine or androgen-deprivation therapeutic drugs (such as luteinizing hormone-releasing analogs and anti-androgen drugs) may interfere with^11C-choline PET imaging. One published report of^18F-methylcholine PET imaging indicated that discontinuation of colchicine for two weeks resolved the colchicine effect. The impact of discontinuation of androgen-deprivation therapy upon^11C-choline PET imaging has not been established [see Drug Interactions (7)].

5.2 Allergic Reactions

As with any injectable drug product, allergic reactions and anaphylaxis may occur. Emergency resuscitation equipment and personnel should be immediately available.

5.3 Radiation Risks

Choline C 11 Injection contributes to a patient’s overall long-term cumulative radiation exposure. Long-term cumulative radiation exposure is associated with an increased risk for cancer. Safe handling should be ensured to minimize radiation exposure to the patient and health care workers [ see Dosage and Administration (2.1)].

6 ADVERSE REACTIONS

Exclusive of an uncommon, mild injection site reaction, no adverse reactions to^11C-choline have been reported.

7 DRUG INTERACTIONS

Colchicine and androgen-deprivation therapeutic drugs have been reported to interfere with choline-based PET imaging [ see Warnings and Precautions (5.1)].

The impact of androgen-deprivation therapeutic drugs upon^11C-choline PET imaging may depend upon the hormonal responsiveness of a patient’s recurrent prostate cancer. Clinical studies have not established this relationship but published reports suggest^11C-choline PET imaging may be productive in patients with “hormone resistant” recurrent prostate cancer even if the patients are receiving anti-androgen therapy. Imaging may prove unproductive or misleading due to failed or insufficient ^11C-choline uptake in patients with hormone-responsive cancer if the patients are receiving androgen-deprivation therapy.

8 USE IN SPECIFIC POPULATIONS

8.1 Pregnancy

Pregnancy Category C.

There are no adequate and well controlled studies with Choline C 11 Injection in pregnant women and the fetal radiation dose from a^11C-choline PET imaging study is unknown. It is not known whether Choline C 11 Injection can cause fetal harm when administered to a pregnant woman or can affect reproduction capacity. Animal reproduction studies have not been conducted with^11C-choline.

All radiopharmaceuticals, including Choline C 11 Injection, have a potential to cause fetal harm. The likelihood of fetal harm depends on the stage of fetal development and the magnitude of the radiopharmaceutical dose. Assess pregnancy status before administering Choline C 11 Injection to a female of child bearing potential. Choline C 11 Injection should be given to a pregnant woman only if clearly needed.

8.3 Nursing Mothers

Choline C 11 Injection is not indicated for use in women. It is not known whether Choline C 11 Injection is excreted in human milk. Because many drugs are excreted in human milk and because of the potential for radiation exposure to nursing infants from Choline C 11 Injection, nursing mothers should use alternative infant nutrition sources (e.g., stored breast milk or infant formula) and pump and discard breast milk for 8 hours (>10 half lives of radioactive decay for^11C isotope) after administration of the drug or avoid use of the drug, taking into account the importance of the drug to the mother.

8.4 Pediatric Use

The safety and effectiveness of Choline C 11 Injection have not been established in pediatric

patients.

11 DESCRIPTION

11.1 Chemical Characteristics

Choline C 11 Injection is a positron emitting radiopharmaceutical that is used for diagnostic purposes in conjunction with PET imaging. The active ingredient,^11C-choline, has the molecular formula of C4^11CH14 NOCl with a molecular weight of 138.63 g and has the following chemical structure:

Choline C 11 Injection is provided as a ready to use sterile, pyrogen-free, clear and colorless solution. Each milliliter contains 148 – 1,225 MBq (4 – 33.1 mCi) of^11C-choline at EOS calibration time in aqueous 0.9% sodium chloride solution. The pH of the solution is between 4.5 and 7.5.

11.2 Physical Characteristics

Carbon 11 is a cyclotron-produced radionuclide that decays to Boron 11 by positron emission and has a physical half life of 20.4 minutes (Table 2).

Table 2: Principal Radiation Emission Data for^11C
Radiation/Emission | % Per Disintegration | Energy
Positron (β+) | 99.76 | 960.2 keV (Max.)
Gamma (±)* | 199.5 | 511 keV

*Produced by positron annihilation

The specific gamma ray constant (point source air kerma coefficient) for^11C-choline is 5.8 R/mCi-hr at 1 cm. Selected coefficients of attenuation are listed in Table 3 as a function of lead shield thickness. For example, the use of 39 mm thickness of lead will attenuate the external radiation by a factor of about 1,000.

Table 3: Radiation Attenuation of 511 keV Photons by lead (Pb) shielding
Shield Thickness (Pb) mm | Coefficient of Attenuation
4 | 0.5
8 | 0.25
13 | 0.1
26 | 0.01
39 | 0.001
52 | 0.0001

Table 4 lists fractions remaining at selected time intervals from the calibration time. This information may be used to correct for physical decay of the radionuclide.

Table 4: Physical Decay Chart for^11C
Minutes | Fraction Remaining
0* | 1.000
5 | 0.844
10 | 0.712
15 | 0.600
20 | 0.507
25 | 0.427
30 | 0.360

*Calibration time

12 CLINICAL PHARMACOLOGY

12.1 Mechanism of Action

Choline C 11 Injection is a radiolabeled analog of choline, a precursor molecule essential for the biosynthesis of cell membrane phospholipids. Choline is involved in synthesis of the structural components of cell membranes, as well as modulation of trans-membrane signaling. Increased phospholipid synthesis (i.e., increased uptake of choline) has been associated with cell proliferation and the transformation process that occurs in tumor cells.

12.2 Pharmacodynamics

In a study of men with prostatic hyperplasia or primary prostate cancer, PET imaging showed^11C-choline radioactivity accumulated rapidly within the prostate; uptake appeared to peak by five minutes following injection of the drug and activity was retained over the subsequent 30 minute scanning period. Little uptake was observed in the bladder and rectum.

12.3 Pharmacokinetics

Distribution: ^11C-choline distributes mainly to the pancreas, kidneys, liver, spleen and colon [ see Dosage and Administration (2.4)]. Based upon the relatively low urinary excretion of radioactivity, renal distribution is predominantly to the organ itself, rather than via formation of urine.

Metabolism: Following intravenous administration,^11C-choline undergoes metabolism resulting in the detection of^11C-betaine as the major metabolite in blood. In a study of patients with prostate cancer or brain disorders, the fractional activities of ^11C-choline and^11C-betaine in human arterial plasma appeared to reach a plateau within 25 minutes, with^11C-betaine representing 82± 9% of the total^11C detected at that time point. A small amount of unmetabolized^11C-choline was detected within the blood at the final sampling time point (40 minutes).

Elimination: Urinary excretion of^11C-choline was < 2% of the injected radioactivity at 1.5 hours after injection of the drug. The rate of^11C-choline excretion in urine was 0.014 mL/min.

13 NONCLINICAL TOXICOLOGY

13.1 Carcinogenesis, Mutagenesis, Impairment of Fertility

Long term studies have not been performed to evaluate the carcinogenic potential of Choline C 11 Injection. The mutagenic potential of Choline C 11 Injection has not been adequately evaluated; however, any radiopharmaceutical, including Choline C 11 Injection, has the potential to be mutagenic. The effect of Choline C 11 Injection on fertility has not been evaluated.

14 CLINICAL STUDIES

A systematic review of published reports identified four studies that contained data sufficient to compare ^11C-choline PET imaging to histopathology (truth standard) among patients with suspected prostate cancer recurrence and non-informative conventional imaging (for most patients, CT or MRI). In general, the suspected recurrence criteria consisted of at least two sequential PSA levels of > 0.2 ng/mL for men who had undergone prostatectomy and PSA levels of ≥ 2 ng/mL above the post-therapy nadir for men who had undergone radiotherapy. The studies were predominantly single clinical site experiences and image acquisition generally surveyed radioactivity distribution from the base of the pelvis to the base of the skull.

Prospective studies: Two studies examined the ability of^11C-choline PET/CT to detect prostate cancer in pelvic and/or retroperitoneal lymph nodes among patients who had previously undergone radical prostatectomy. Both studies used a truth standard of lymph node histopathology.^11C-choline images were interpreted by readers masked to clinical information; surgical resection of lymph nodes was performed by surgeons aware of the^11C-choline PET/CT results.

In Study One^3, 25 patients who underwent^11C-choline PET/CT and conventional imaging (CT or MRI) were scheduled to undergo pelvic or pelvic plus retroperitoneal lymphadenectomy following the imaging identification of suspected lymph node metastases. The median PSA was 2.0 ng/mL (range 0.2 to 23.1 ng/mL). The study excluded subjects with metastatic disease detected by bone scintigraphy or isolated prostatic fossa recurrence. Among the 25 patients, 21 had positive^11C-choline PET/CT scans; histopathology verified cancer in 19 of these patients. Lymph node histopathology detected no cancer among the four patients who had surgery based only on positive conventional imaging;^11C-choline PET/CT was negative in all four patients. The study report included information for patients who had non-informative conventional imaging (CT or MRI, bone scintigraphy and transrectal ultrasound), as shown in Table 5.

In Study Two^4, 15 patients were scheduled to undergo pelvic or pelvis plus retroperitoneal lymphadenectomy solely based upon positive^11C-choline PET/CT imaging in the setting of negative conventional imaging (ultrasound and/or CT and/or MRI and/or bone scintigraphy). The median PSA was 2.0 ng/mL (range 1.0 to 8.0 ng/mL); all patients had previously undergone radical prostatectomy. Eight of the 15 patients had cancer verified by lymph node histology; histology detected no cancer in seven patients.

Retrospective Studies: Two studies were retrospective reviews of patients who underwent^11C-choline PET/CT and had histopathology obtained from biopsy of the prostatic fossa or other suspected recurrence sites.

In Study Three^5,^11C-choline PET/CT imaging was performed among 36 patients with suspected prostate cancer recurrence and 13 subjects without suspected recurrence (controls). Prostatic fossa biopsies were performed among the patients with suspected recurrence. All the patients and control subjects had previously undergone radical prostatectomy; patient with suspected recurrence had no evidence of cancer using conventional clinical evaluations, including trans-rectal ultrasound and bone scintigraphy. PET/CT scans were interpreted by readers masked to clinical information. Median PSA was 2.0 ng/mL (range 0.3 – 12.1 ng/mL) for patients with suspected recurrence and 0.1 ng/mL (range 0.0 – 0.2 ng/mL) in control subjects. Prostatic fossa biopsy showed cancer in 33 of the 36 patients with suspected recurrence. PET/CT scans were positive in 25 of the 36 patients; two patients had false positive scans (one scan in a control subject and one scan in a suspected recurrence subject who had no cancer detected on prostatic fossa biopsy). Among the 13 control subjects, 12 had negative PET/CT scans.

In Study Four^6,7, 34 patients with negative conventional imaging underwent^11C-choline PET/CT and subsequently had biopsies of suspected recurrence sites. The median PSA level of the 34 patients was 3.9 ng/mL (range 0.2 – 65.0 ng/mL); 22 of the patients had previously undergone radical prostatectomy and 12 had received other therapy (radiotherapy, anti-androgen therapy or cryotherapy).^11C-choline PET/CT images were positive in 30 patients and negative in four patients. Cancer was verified by histopathology in 29 patients; 25 had positive PET/CT images and four had negative PET/CT images. Five patients with positive PET/CT images did not have cancer confirmed with histopathology.

As shown in Table 5, within each study at least half the patients with non-informative conventional imaging had positive^11C-choline PET/CT images and histologically verified recurrent prostate cancer.

Table 5 ^11 C-Choline PET/CT Results among Patients with Non-informative Conventional Imaging and a Histopathology Truth Standard
Study | Patients, n
 | Total | True Positive | False Positive | True Negative | False Negative
One | 13 | 11 | 2 | ND* | ND*
Two | 15 | 8 | 7 | ND* | ND*
Three | 36 | 23 | 1 | 2 | 10
Four | 34 | 25 | 5 | 0 | 4

*ND = not determined

In Studies Three and Four, PSA levels were generally lower for patients with negative^11 C-choline PET/CT results than for patients with positive results. In Study Three, the median PSA was 2.6 ng/mL (range 0.6 – 12.1 ng/mL) among the 23 patients with true positive images; nine out of 11 patients with false negative or false positive images had PSA levels < 2 ng/mL. In Study Four, the median PSA was 4.2 ng/mL (range 0.2 – 65.0 ng/mL) among the 25 patients with true positive images; PSA levels < 2 ng/mL were observed in four of the nine patients with false negative or false positive images. These data, combined with other published reports, suggest that ^11C-choline PET imaging performance may be more reliable among patients with blood PSA levels > 2 ng/mL, compared to patients with lower levels.

15 REFERENCES

^1Tolvanen T, Yli-Kerttula T, Ujula T, Autio A, Lehikoinen P, Minn J, RoivinenA; Biodistribution and radiation dosimetry of [^11C] choline: a comparison between rat and human data. Eur J Nucl Med Mol Imaging. 2010; 37:874-83.

^2OLINDA/EXM software, Version 1.1. Vanderbilt University, 2007.

^3Scattoni V, Picchio M, Suardi N, Messa C, Freschi M, Roscigno M, Da Pozzo L, Bocciardi A, Rigatti P, Fazio F. Detection of lymph-node metastases with integrated [^11C]choline PET/CT in patients with PSA failure after radical retropubic prostatectomy: results confirmed by open pelvic-retroperitoneal lymphadenectomy. Eur Urol. 2007; 52:423-9.

^4Rinnab L, Mottaghy FM, Simon J, Volkmer BG, de Petriconi R, Hautmann RE, Wittbrodt M, Egghart G, Moeller P, Blumstein N, Resks S, Kuefer R. [^11C]choline PET/CT for targeted salvage lymph node dissection in patients with biochemical recurrence after primary curative therapy for prostate cancer. Urologia Int. 2008; 81:191-7.

^5Reske SN, Blumstein NM, Glatting G. [^11C]choline PET/CT imaging in occult local relapse of prostate cancer after radical prostatectomy. Eur J Med Mol Imaging. 2008; 35:9-17.

^6Mitchell C, Kwon E, Lowe V, Hung J, Rangel L, Karnes RJ. Impact of 11C-choline PET/CT scan on detection of recurrent prostate cancer in men with biochemical recurrence following failed initial treatment; supplemented with subject-level data. J Urol. 2012; 187:e823.

^7Mitchell C, Kwon E, Lowe V, Hung J, Rangel L, Karnes RJ. Detection of consolidated disease recurrences of prostate cancer by 11C-choline PET/Scan: results confirmed by surgical resection; supplemented with subject-level data. J Urol. 2012; 187:e823.

16 HOW SUPPLIED/STORAGE AND HANDLING

16.1 How Supplied

Choline C 11 Injection is packaged in a single dose glass vial containing between 148 MBq to 1,225 MBq (4 mCi to 33.1 mCi) per milliliter of^11C-choline at EOS calibration time in aqueous 0.9% sodium chloride solution.

16.2 Storage and Handling

Store Choline C 11 Injection at 25°C (77°F); excursions permitted to 15 – 30°C (59 – 86°F) (see USP Controlled Room Temperature). Use the solution within 120 minutes of EOS calibration.

17 PATIENT COUNSELING INFORMATION

- Instruct patients to drink plenty of water or other fluids (as tolerated) in the four hours before their PET/CT study.
- Instruct patients to void after completion of each image acquisition session and as often as possible for one hour after the PET/CT scan ends.

Manufactured by:

Mayo Clinic PET Radiochemistry Facility
200 1st St SW
Rochester, MN 55905

Mayo Clinic PET Radiochemistry Facility
5861 E Mayo Blvd
Phoenix, AZ 85054

Distributed by:

Mayo Clinic PET Radiochemistry Facility
200 1st St SW
Rochester, MN 55905

Mayo Clinic PET Radiochemistry Facility
5861 E Mayo Blvd
Phoenix, AZ 85054

PACKAGE LABEL

PRINCIPAL DISPLAY PANEL

NDC# 52670-556-30
Choline C 11 Injection
For Intravenous Use Rx Only